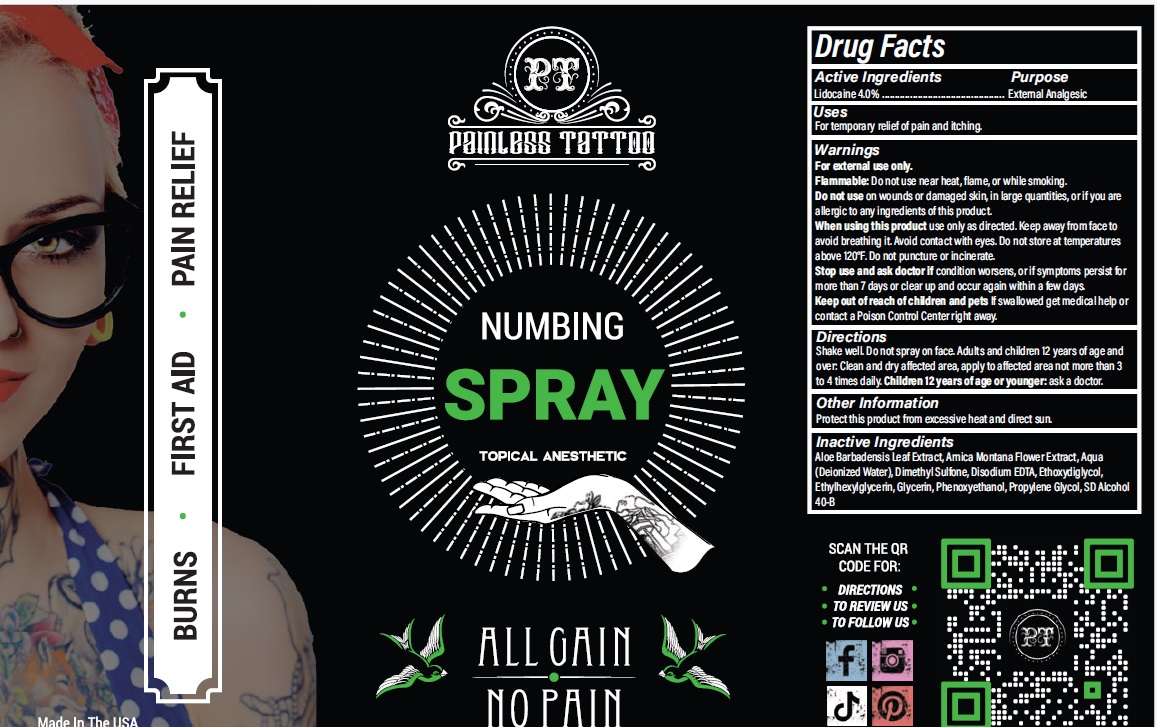 DRUG LABEL: Painless Tattoo Numbing
NDC: 54723-019 | Form: LIQUID
Manufacturer: Sambria Pharmaceuticals, LLC
Category: otc | Type: HUMAN OTC DRUG LABEL
Date: 20251112

ACTIVE INGREDIENTS: LIDOCAINE HYDROCHLORIDE 4 g/100 mL
INACTIVE INGREDIENTS: WATER; ALCOHOL; ALOE VERA LEAF; DIMETHYL SULFONE; PROPYLENE GLYCOL; DIETHYLENE GLYCOL MONOETHYL ETHER; ARNICA MONTANA FLOWER; GLYCERIN; PHENOXYETHANOL; EDETATE DISODIUM; ETHYLHEXYLGLYCERIN

Active ingredient

Lidocaine HCL 4.0%

Purpose

External Analgesic

Uses

For temporary relief of pain and itching.

Warnings

For external use only.

Flammable: Do not use near heat, flame, or while smoking.

Do not useon wounds or damaged skin, in large quantities, or if you are allergic to any ingredients of this product.

When using this productuse only as directed. Keep away from face to avoid breathing it. Avoid contact with eyes. Do not store at temperatures above 120°F. Do not puncture or incinerate.

Stop use and ask doctor ifcondition worsens, or if symptoms persist for more than 7 days or clear up and occur again within a few days.

Keep out of reach of childrenand pets If swallowed get medical help or contact a Poison Control Center right away.

Directions

Shake well. Do not spray on face. Adults and children 12 years of age and over: Clean and dry affected area, apply to affected area not more than 3 to 4 times daily. Children 12 years of age or younger: ask a doctor.

Other Information

Protect this product from excessive heat and direct sun.

Inactive Ingredients

Aloe Barbadensis Leaf Extract, Arnica Montana Flower Extract, Aqua (Deionized Water), Dimethyl Sulfone, Disodium EDTA, Ethoxydiglycol, Ethylhexylglycerin, Glycerin, Phenoxyethanol, Propylene Glycol, SD Alcohol 40-B